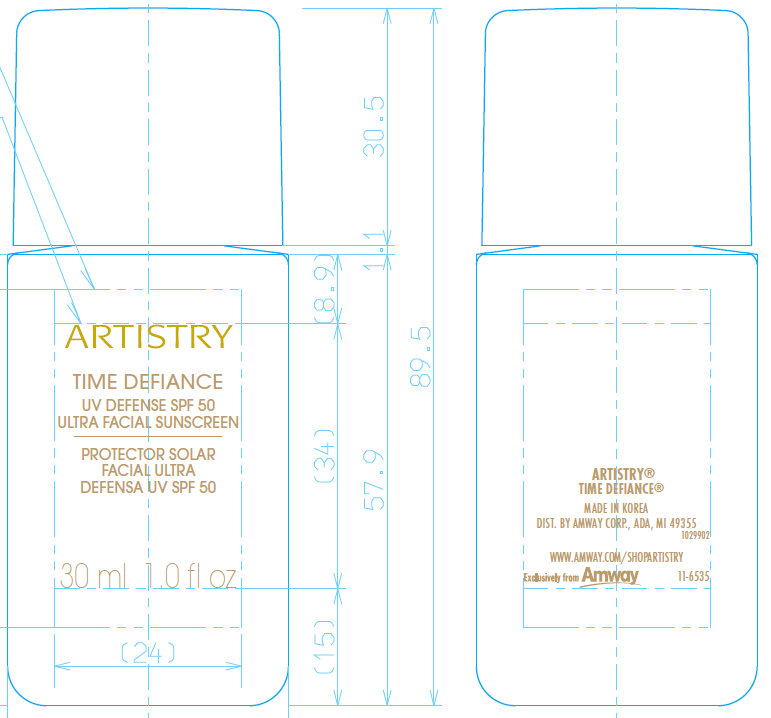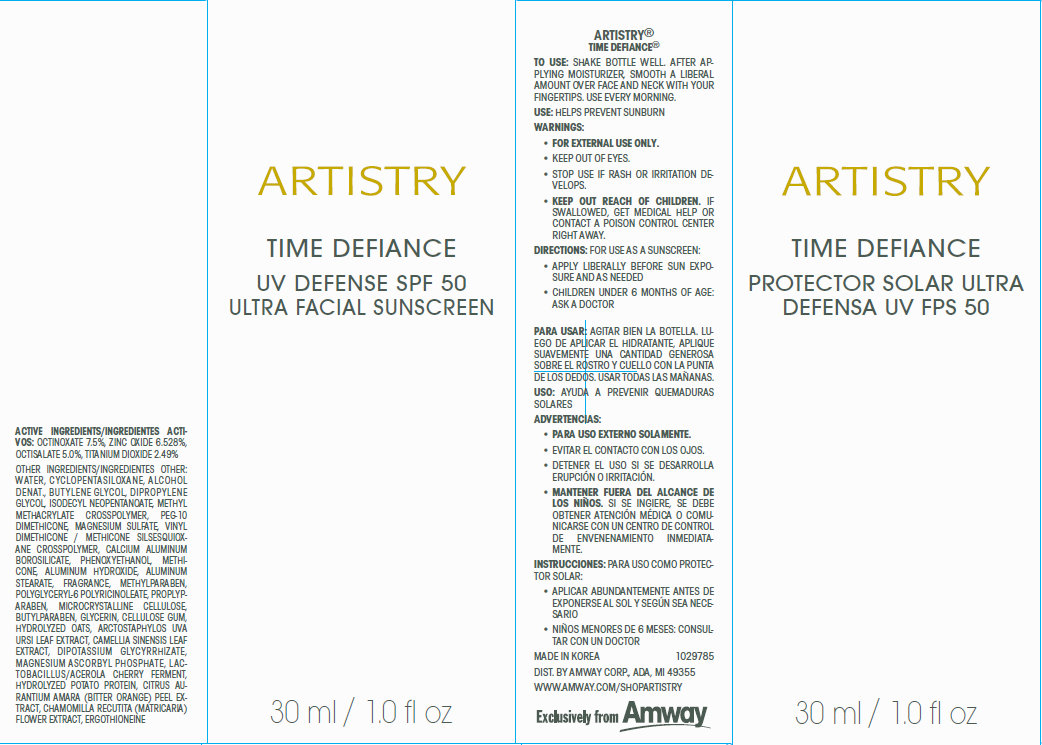 DRUG LABEL: ARTISTRY Time Defiance UV Defense SPF 50 Ultra Facial Sunscreen
NDC: 50390-110 | Form: CREAM
Manufacturer: Amway Corp
Category: otc | Type: HUMAN OTC DRUG LABEL
Date: 20120517

ACTIVE INGREDIENTS: OCTINOXATE 7.5 mL/100 mL; ZINC OXIDE 6.528 mL/100 mL; OCTISALATE 5 mL/100 mL; TITANIUM DIOXIDE 2.49 mL/100 mL
INACTIVE INGREDIENTS: WATER; CYCLOMETHICONE 5; BUTYLENE GLYCOL; DIPROPYLENE GLYCOL; ISODECYL NEOPENTANOATE; METHYL METHACRYLATE; MAGNESIUM SULFATE; CALCIUM ALUMINOSILICATE; PHENOXYETHANOL; METHICONE (20 CST); ALUMINUM HYDROXIDE; ALUMINUM STEARATE; METHYLPARABEN; PROPYLPARABEN; CELLULOSE, MICROCRYSTALLINE; BUTYLPARABEN; GLYCERIN; CARBOXYMETHYLCELLULOSE SODIUM; OAT; ARCTOSTAPHYLOS UVA-URSI LEAF; GREEN TEA LEAF; GLYCYRRHIZINATE DIPOTASSIUM; MAGNESIUM ASCORBYL PHOSPHATE; ACEROLA; POTATO; CITRUS AURANTIUM FRUIT RIND; CHAMOMILE; ERGOTHIONEINE

ARTISTRY Time Defiance UV Defense SPF 50 Ultra Facial Sunscreen

Active Ingredients

OCTINOXATE 7.5%, ZINC OXIDE 6.528%, OCTISALATE 5.0%, TITANIUM DIOXIDE 2.49%

Other Ingredients

WATER , CYCLOPENTASILOXANE , ALCOHOL DENAT., BUTYLENE GLYCOL, DIPROPYLENE GLYCOL, ISODECYL NEOPENTANOATE, METHYL METHACRYLATE CROSSPOLYMER, PEG-10 DIMETHICONE, MAGNESIUM SULFATE, VINYL DIMETHICONE / METHI CONE SILSESQUIOXANE CROSSPOLYMER, CALCIUM ALUMINUM BOROSILI CATE , PHENOXYETHANOL , METHICONE , ALUMINUM HYDROXIDE , ALUMINUM STEARATE, FRAGRANCE, METHYLPARABEN, POLYGLY CERYL -6 POLYRI CINOLEATE , PROPLYPARABEN, MICROCRYSTALLINE CELLULOSE, BUTYLPARABEN, GLYCERIN, CELLULOSE GUM, HYDROLYZED OATS, ARCTOSTAPHYLOS UVA
URSI LEAF EXTRA CT, CAMELLIA SINENSIS LEAF EXTRA CT, DIPOTASSIUM GLY CYRRHI ZATE, MAGNESIUM ASCORBYL PHOSPHATE, LACTOBACILLUS/ ACEROLA CHERRY FERMENT, HYDROLYZED POTATO PROTEIN, CITRUS AURANTIUM AMARA (BITTER ORANGE) PEEL EXTRACT, CHAMOMILLA RECUTITA (MATRICARIA), FLOWER EXTRACT, ERGOTHIONEINE

To Use:

SHAKE BOTTLE WELL. AFTER APPLYING MOISTURIZER, SMOOTH A LIBERAL AMOUNT OVER FACE AND NECK WITH YOUR FINGERTIPS. USE EVERY MORNING.

Use:

Helps prevent sunburn

Warnings:

- For external use only.
- Keep out of eyes.
- Stop use if rash or irritation develops
- Keep out reach of children. If swallowed, get medical help or contact a Poison Control Center right away .

Directions:

For use as a sunscreen:
• Apply liberally before sun exposure and as needed
• Children under 6 months of age: Ask a doctor

ARTISTRY® TIME DEFIANCE® UV DEFENSE SPF 50 ULTRA FACIAL SUNSCREEN

Help keep your skin looking younger longer by protecting it with this high-level sunscreen. Moisturizing and fast absorbing, it works during the highest levels of sun exposure to deflect damaging rays and environmental assaults.

Shields skin against dark spots and discoloration. An exclusive Balanced Brightening Complex of 10 extracts, including white tea extract, helps give your skin a luminous glow. This lightweight, water-resistant formula creates the perfect base for makeup to glide on.

To use: Shake bottle well. After applying moisturizer, smooth a liberal amount over face and neck with your fingertips. Use every morning.

Smooth on as the final step in your ARTISTRY TIME DEFIANCE skincare regimen and before applying foundation.

Dermatologist- and allergy-tested. Suitable for use on sensitive skin. Non-acnegenic.